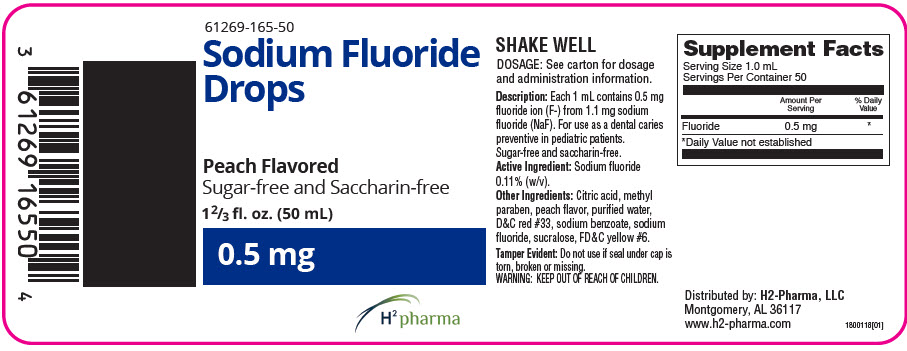 DRUG LABEL: Sodium Fluoride Drops
NDC: 61269-165 | Form: SOLUTION/ DROPS
Manufacturer: H2-Pharma, LLC
Category: other | Type: DIETARY SUPPLEMENT
Date: 20250916

ACTIVE INGREDIENTS: SODIUM FLUORIDE 0.5 mg/1 mL
INACTIVE INGREDIENTS: CITRIC ACID MONOHYDRATE; METHYLPARABEN; PEACH; WATER; D&C RED NO. 33; SODIUM BENZOATE; SUCRALOSE; FD&C YELLOW NO. 6

Sodium Fluoride Drops

STATEMENT OF IDENTITY

Supplement Facts
Serving Size 1.0 mL
Servings Per Container 50
 | Amount Per Serving | % Daily Value
Fluoride | 0.5 mg | [Daily Value not established]

*U.S. Recommended Daily Allowance not established. Consult your physician for use by infants and children under 2 years of age.

Active Ingredient: Sodium fluoride 0.11% (w/v).

Other Ingredients: Citric acid, methyl paraben, peach flavor, purified water, red #33, sodium benzoate, sodium fluoride, sucralose, yellow #6.

These statements have not been evaluated by the FDA. This product is not intended to diagnose, treat, cure or prevent any disease.

HEALTH CLAIM

DOSAGE SCHEDULE [Conforms to new ADA and AAP guidelines for supplementation.] WATER F CONTENT
AGE | 0-0.3 PPM | 0.3-0.6 PPM | > 0.6 PPM
6 months to 3 years | 0.25 mg F = 1/2 mL = Half dropperful | 0 | 0
3-6 years | 0.5 mg F = 1 mL = One dropperful | 0.25 mg F = 1/2 mL = Half dropperful | 0
6-16 years | 1 mg F = 2 mL = Two dropperfuls | 0.5 mg F = 1 mL = One dropperful | 0

Description

Each 1 mL contains 0.5 mg fluoride ion (F-) from 1.1 mg of sodium fluoride (NaF). For use as a dental caries preventative in pediatric patients. Sugar-free and saccharin-free. Active Ingredient: Sodium fluoride 0.11% (w/v). Other Ingredients: Citric acid, methyl paraben, peach flavor, purified water, red #33, sodium benzoate, sodium fluoride, sucralose, yellow #6.

KEEP THIS AND ALL MEDICATIONS OUT OF THE REACH OF CHILDREN.

CLINICAL PHARMACOLOGY

Sodium fluoride acts systemically (before tooth eruption) and topically (post eruption) by increasing tooth resistance to acid dissolution, by promoting demineralization and by inhibiting the cariogenic microbial process.

USAGE

It has been established that ingestion of fluoridated drinking water (1 ppm F) during the period of tooth development results in significant decrease in the incidence of dental caries. Sodium Fluoride Drops 0.5 mg were developed to provided systemic fluoride for use as a supplement for patients living in areas where the drinking water fluoride level does not exceed 0.6 ppm F. See guidelines for supplementation from ADA and AAP.

CONTRAINDICATIONS

Do not use in areas where drinking water exceed 0.6 ppm F. Do not administer to patients less than 6 months old.

WARNINGS

See "CONTRAINDICATIONS" above.

PRECAUTIONS

See "OVERDOSAGE" section. Incompatibility of fluoride with dairy foods has been reported due to formation of calcium fluoride which is poorly absorbed. Not for ophthalmic use.

ADVERSE REACTIONS

Allergic rash or other idiosyncrasies have been rarely reported. To report SUSPECTED ADVERSE REACTIONS, contact H2-Pharma at 1-866-592-6438 or the FDA at 1-800-FDA-1088 or www.fda.gov/med-watch.

OVERDOSAGE

Prolonged daily ingestion of excessive fluoride will result in varying degrees of dental fluorosis. For safety purposes, the total amount of sodium fluoride in a 50 mL bottle of Sodium Fluoride Drops 0.5 mg (25 mg F) conforms with the recommendations of the American Dental Association for the maximum to be dispended at one time.

DOSAGE AND ADMINISTRATION

Daily oral dose: (in areas where the drinking water contains less than 0.3 ppm F): 6 months to age 3: one-half dropperful (1/2 mL); age 3-6, one dropperful (1 mL); age 6-16, two dropperfuls (2 mL). When drinking water is partially fluoridated (0.3 to 0.6 ppm F inclusive) dose as follows: 6 months to age 3, fluoride supplementation not indicated; age 3-6, one-half dropperful (1/2 mL); age 6-16, one dropperful (1 mL) [Conforms to new ADA and AAP guidelines for supplementation.]

HOW SUPPLIED

Sodium Fluoride Drops 0.5 mg are available in 50 mL bottles with an accompanying calibrated dropper.

TAMPER EVIDENT

Do not accept if printed bottle seal around cap is broken or missing.

*REFERENCES

Accepted Dental Therapeutics, Ed. 40. American Dental Association, Chicago, 1984, p.339-402. Jakush, J, New Fluoride schedule adopted. ADA New, May 16, 1994, p. 12, 14.

RECOMMENDED STORAGE

Store at controlled room temperature, 20°-25°C (68°-77°F) [See USP Controlled Room Temperature]. After opening, store away from direct light. Close tightly after each use. REFRIGERATION IS NOT REQUIRED.

HEALTH CLAIM

Distributed by: H2-Pharma, LLC
2010 Berry Chase Place, Montgomery, AL 36117
www.h2-pharma.com

PRINCIPAL DISPLAY PANEL - 50 mL Bottle Label

61269-165-50

Sodium Fluoride
Drops

Peach Flavored
Sugar-free and Saccharin-free

1⅔ fl. oz. (50 mL)

0.5 mg

H^2 pharma